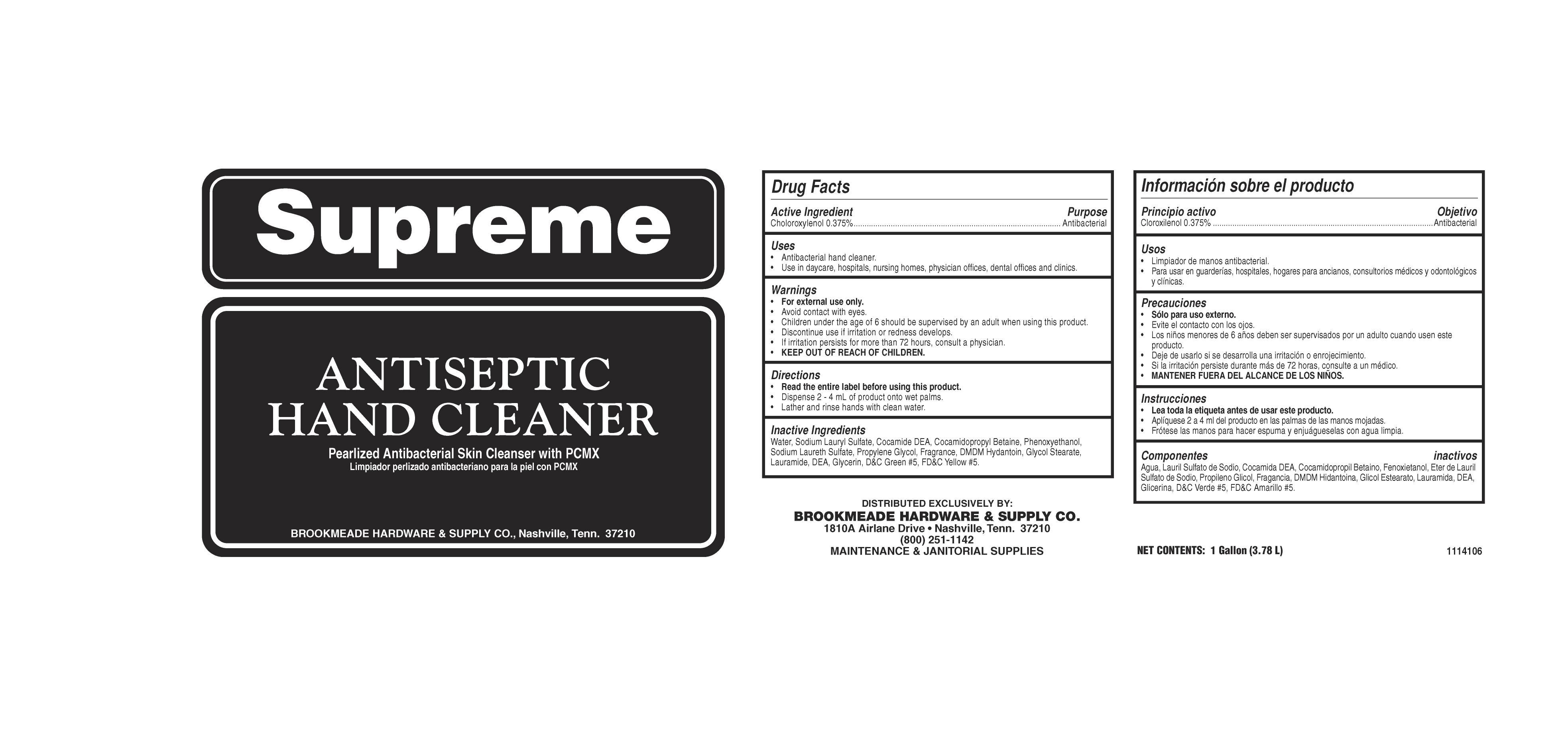 DRUG LABEL: Supreme
NDC: 68304-141 | Form: SOAP
Manufacturer: Brookmeade Hardware & Supply Co.
Category: otc | Type: HUMAN OTC DRUG LABEL
Date: 20130219

ACTIVE INGREDIENTS: CHLOROXYLENOL 3.75 mg/1 mL
INACTIVE INGREDIENTS: WATER; SODIUM LAURYL SULFATE; COCO DIETHANOLAMIDE; COCAMIDOPROPYL BETAINE; PHENOXYETHANOL; PROPYLENE GLYCOL; DMDM HYDANTOIN; GLYCOL STEARATE; LAURIC DIETHANOLAMIDE; GLYCERIN; D&C GREEN NO. 5; FD&C YELLOW NO. 5

Supreme

Supreme

Active Ingredient

Chloroxylenol 0.375%

Supreme

Uses

- Antibacterial hand cleaner.
- Use in daycare, hospitals, nursing homes, physicians offices, dental offices and clinics

Supreme

Warnings

- For external use only.
- Avoid contact with eyes.
- Children under the age of 6 should be supervised by an adult when using this product.
- Discontinue use is irritation or redness develops.
- If irritation persists for more than 72 hours, consult a physician.
- KEEP OUT OF REACH OF CHILDREN.

Supreme

Directions

- Read the entire label before using this product.
- Dispense 1-2 pumps of product onto wet palm.
- Lather and rinse hands with clean water

Supreme

Inactive Ingredients

Water, Sodium Lauryl lSulfate, Cocamide DEA, Cocamidopropyl betadine, Phenoxyethanol, Sodium Laureth Sulfate, Propylene Glycol, Fragrance, DMDM Hydantoin, Glycol Stearate, Laurimide DEA, Glycerine, Tocopheryl Acetate, D&C Green #5, FD&C Yellow #5.

Supreme

Purpose

Antibacterial

Supreme

KEEP OUT OF REACH OF CHILDREN

Supreme

Antiseptic Hand Cleaner

Pearlized Antibacterial Skin Cleanser with PCMX

BROOKMEADE HARDWARE & SUPPLY CO., Nashville, Tenn. 37210